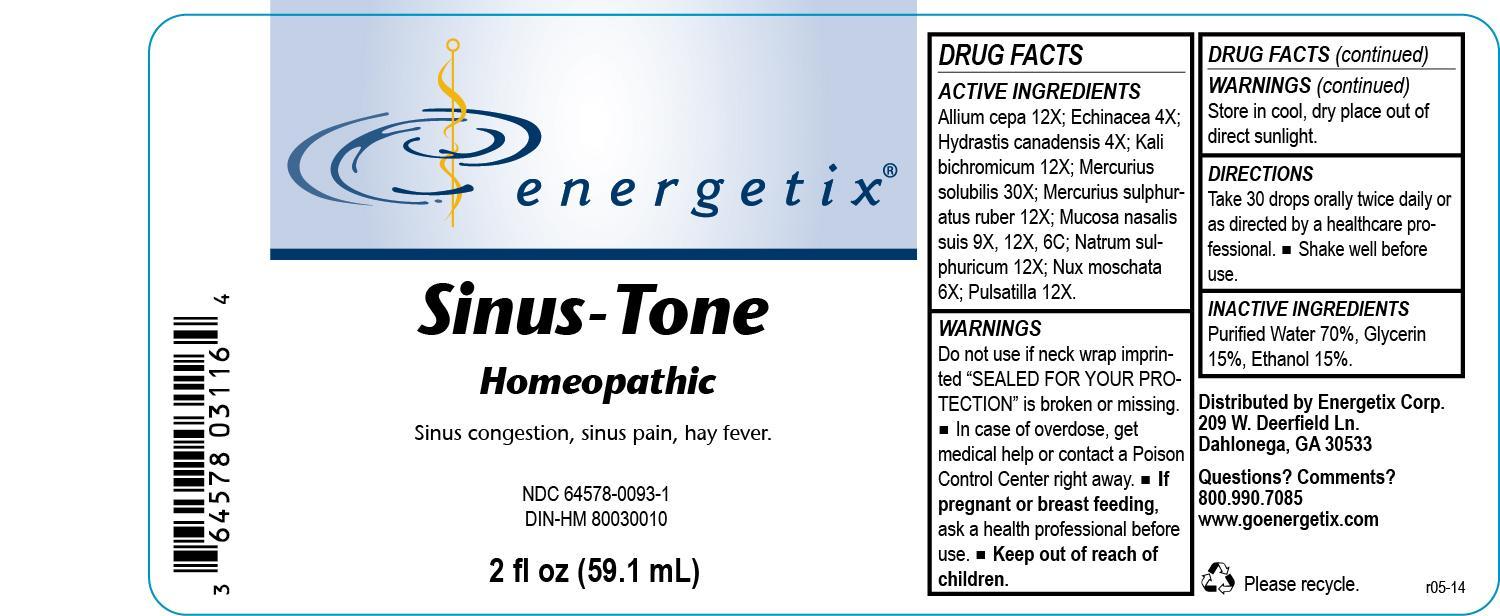 DRUG LABEL: Sinus-Tone
NDC: 64578-0093 | Form: LIQUID
Manufacturer: Energetix Corp
Category: homeopathic | Type: HUMAN PRESCRIPTION DRUG LABEL
Date: 20140226

ACTIVE INGREDIENTS: onion 12 [hp_X]/59.1 mL; MERCURIC SULFIDE 12 [hp_X]/59.1 mL; ECHINACEA ANGUSTIFOLIA 4 [hp_X]/59.1 mL; goldenseal 4 [hp_X]/59.1 mL; POTASSIUM DICHROMATE 12 [hp_X]/59.1 mL; MERCURIUS SOLUBILIS 30 [hp_X]/59.1 mL; NUTMEG 6 [hp_X]/59.1 mL; PULSATILLA VULGARIS 12 [hp_X]/59.1 mL; SODIUM SULFATE 12 [hp_X]/59.1 mL; SUS SCROFA NASAL MUCOSA 9 [hp_X]/59.1 mL
INACTIVE INGREDIENTS: WATER 41.359658 mL/59.1 mL; ALCOHOL 8.862784 mL/59.1 mL; GLYCERIN 8.862784 mL/59.1 mL

Sinus-Tone

ACTIVE INGREDIENT

Allium cepa 12X; Echinacea 4X; Hydrastis canadensis 4X; Kali bichromicum 12X; Mercurius solubilis 30X; Mercurius sulphuratus ruber 12X; Mucosa nasalis suis 9X, 12X, 6C; Natrum sulphuricum 12X; Nux moschata 6X; Pulsatilla 12X

Do not use if neck wrap imprinted "SEALED FOR YOUR PROTECTION" is broken or missing.

OVERDOSAGE

In case of overdose, get medical help or contact a Poison Control Center right away.

PREGNANCY OR BREAST FEEDING

If pregnant or breast feeding, ask a health professional before use.

Keep out of reach of children.

STORAGE AND HANDLING

Store in cool, dry place out of direct sunlight.

Questions? Comments?

800.990.7085 www.goenergetix.com

PURPOSE

Sinus congestion, sinus pain, hay fever.

INACTIVE INGREDIENT

Purified Water 70%, Glycerin 15%, Ethanol 15%.

DOSAGE AND ADMINISTRATION

Take 30 drops orally twice daily or as directed by a healthcare professional. Shake well before use.

INDICATIONS AND USAGE

Sinus congestion, sinus pain, hay fever.